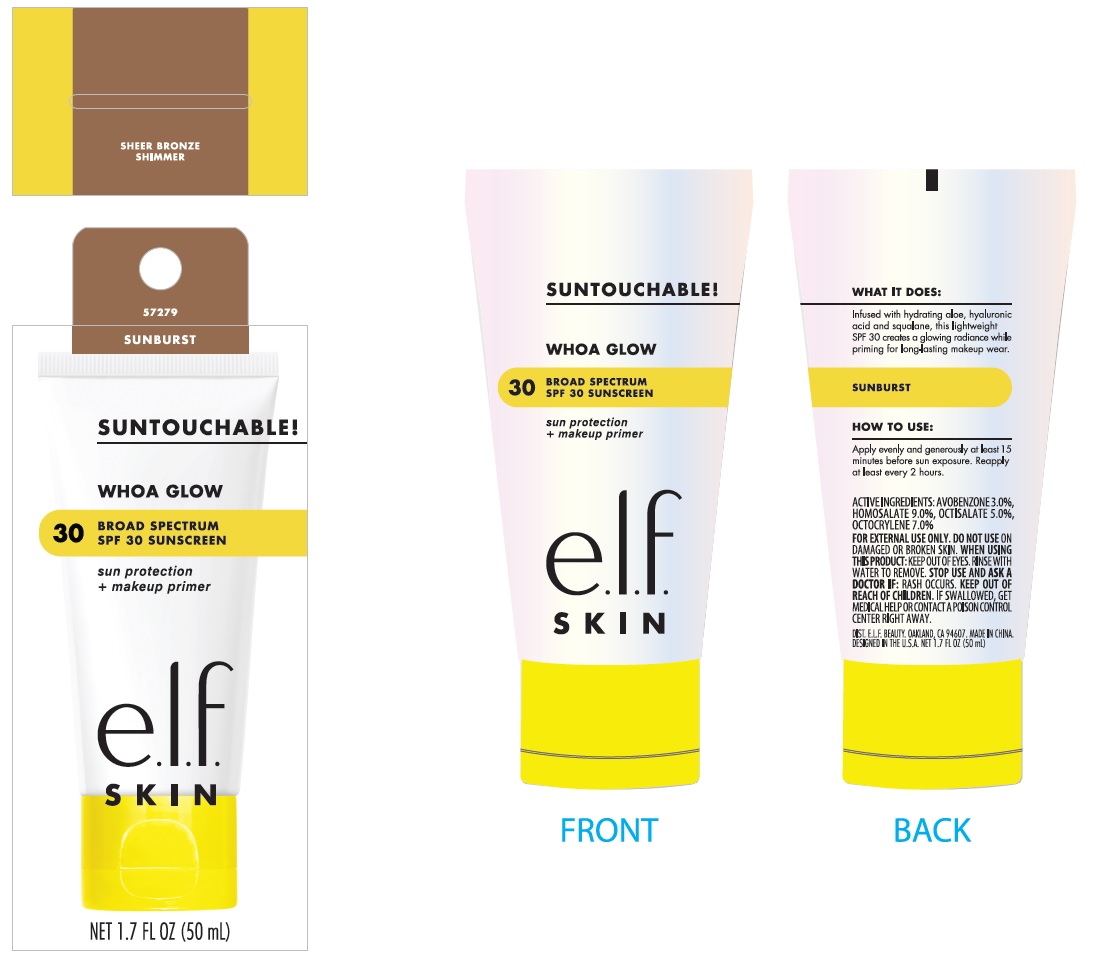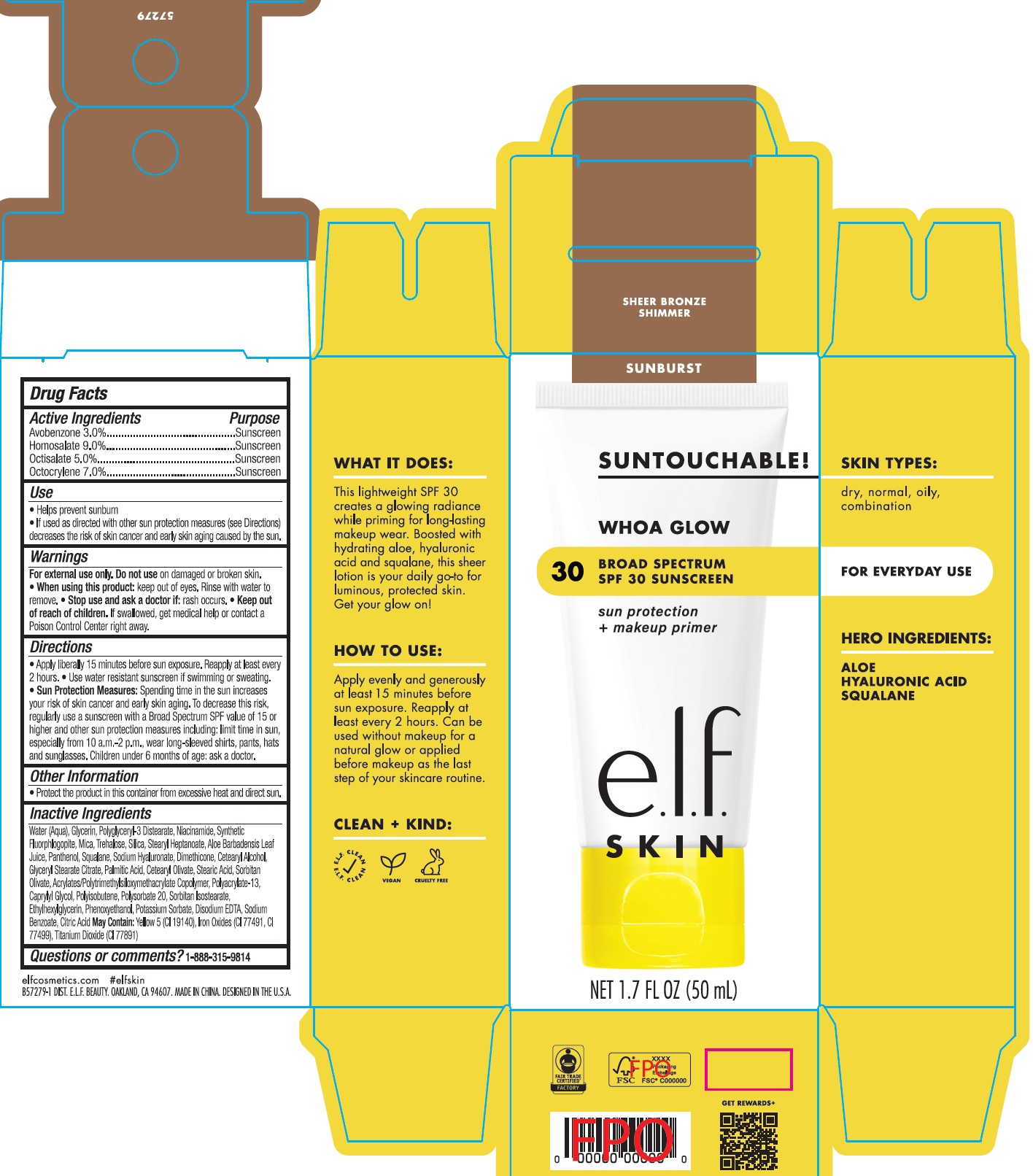 DRUG LABEL: Whoa Glow broad spectrum spf 30 sunscreen Sheer Bronze shimmer
NDC: 76354-445 | Form: CREAM
Manufacturer: e.l.f. Cosmetics, Inc
Category: otc | Type: HUMAN OTC DRUG LABEL
Date: 20241205

ACTIVE INGREDIENTS: AVOBENZONE 30 mg/1 mL; HOMOSALATE 90 mg/1 mL; OCTISALATE 50 mg/1 mL; OCTOCRYLENE 70 mg/1 mL
INACTIVE INGREDIENTS: HYALURONATE SODIUM; DIMETHICONE; CETOSTEARYL ALCOHOL; GLYCERYL STEARATE CITRATE; PALMITIC ACID; CETEARYL OLIVATE; STEARIC ACID; SORBITAN OLIVATE; POLYACRYLATE-13; CAPRYLYL GLYCOL; POLYSORBATE 20; SORBITAN ISOSTEARATE; ETHYLHEXYLGLYCERIN; PHENOXYETHANOL; POTASSIUM SORBATE; EDETATE DISODIUM ANHYDROUS; SODIUM BENZOATE; CITRIC ACID MONOHYDRATE; WATER; GLYCERIN; POLYGLYCERYL-3 DISTEARATE; NIACINAMIDE; MICA; TREHALOSE; SILICON DIOXIDE; STEARYL HEPTANOATE; ALOE VERA LEAF; PANTHENOL; SQUALANE

Whoa Glow broad spectrum spf 30 sunscreen Sheer Bronze shimmer

Active Ingredients

Avobenzone 3.0%

Homosalate 9.0%

Octisalate 5.0%

Octocrylene 7.0%

Purpose

Sunscreen

Use

- Helps prevent sunburn
- If used as directed with other sun protection measures (see Directions) decreases the risk of skin cancer and early skin aging caused by the sun.

Warnings

For external use only.

Do not use

on damaged or broken skin.

When using thsi product:

- keep out of eyes. Rinse with water to remove.

Stop use and ask a doctor if:

- rash occurs.

Keep out of reach of children.

If swallowed, get medical help or contact a Poison Control Center right away.

Directions

- Apply liberally 15 minutes before sun exposure. Reapply at least every 2 hours.
- Use water resistant sunscreen if swimming or sweating.
- Spending time in the sun increases your risk of skin cancer and early skin aging. To decrease this risk, regularly use a sunscreen with a Broad Spectrum SPF value of 15 or higher and other sun protection measures including: limit time in sun, especially from 10 a.m.-2 p.m., wear long-sleeved shirts, pants, hats and sunglasses. Children under 6 months of age: ask a doctor. Sun Protection Measures:

Other Information

- Protect the product in this container from excessive heat and direct sun.

Inactive Ingredients

Water (Aqua), Glycerin, Polyglyceryl-3 Distearate, Niacinamide, Synthetic Fluorphlogopite, Mica, Trehalose, Silica, Stearyl Heptanoate, Aloe Barbadensis Leaf Juice, Panthenol, Squalane, Sodium Hyaluronate, Dimethicone, Cetearyl Alcohol, Glyceryl Stearate Citrate, Palmitic Acid, Cetearyl Olivate, Stearic Acid, Sorbitan Olivate, Acrylates/Polytrimethylsiloxymethacrylate Copolymer, Polyacrylate-13, Caprylyl Glycol, Polyisobutene, Polysorbate 20, Sorbitan Isostearate, Ethylhexylglycerin, Phenoxyethanol, Potassium Sorbate, Disodium EDTA, Sodium Benzoate, Citric Acid May Contain: Yellow 5 (CI 19140), Iron Oxides (CI 77491), CI 77499), Titanium Dioxide (CI 77891)

Questions or comments?

1-888-315-9814